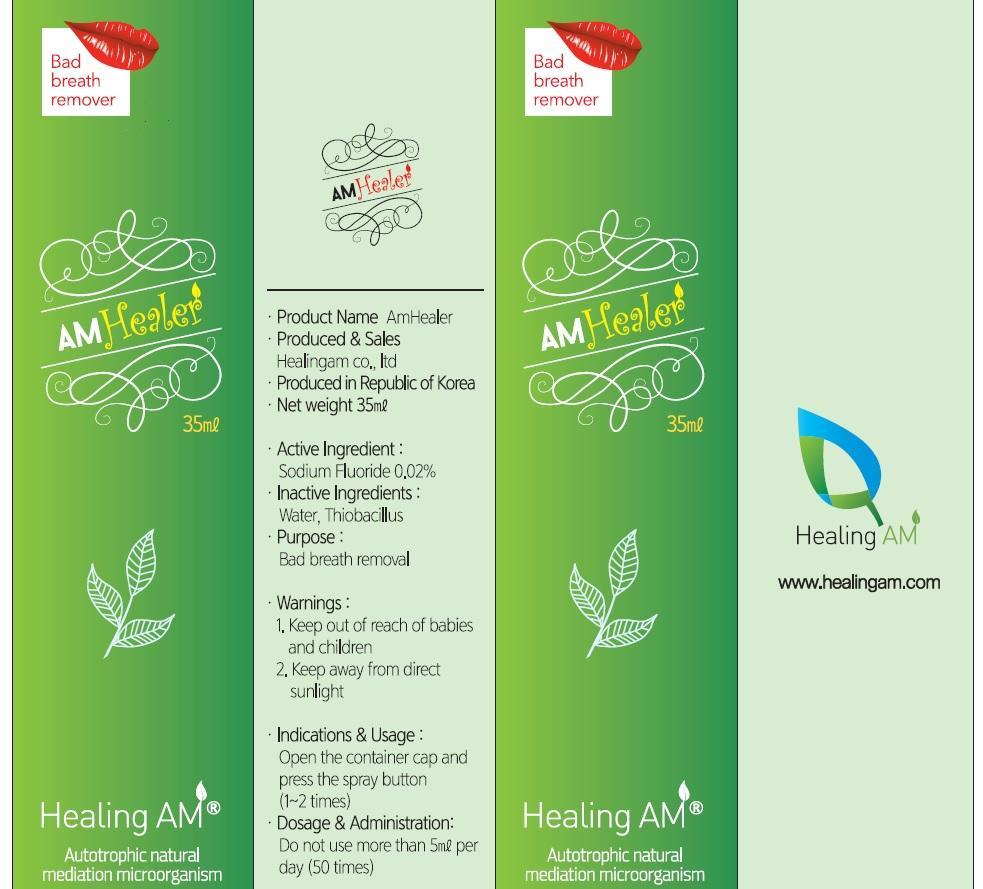 DRUG LABEL: AMHEALER
NDC: 69890-010 | Form: SPRAY
Manufacturer: HEALINGAM CO., LTD
Category: otc | Type: HUMAN OTC DRUG LABEL
Date: 20150623

ACTIVE INGREDIENTS: Sodium Fluoride 0.007 mg/35 mL
INACTIVE INGREDIENTS: Water

ACTIVE INGREDIENT

Active Ingredient: Sodium Fluoride 0.02%

INACTIVE INGREDIENT

Inactive Ingredients: Water, Thiobacillus

PURPOSE

Purpose: Bad breath removal

WARNINGS

Warnings: 1. Keep out of reach of babies and children 2. Keep away from direct sunlight

KEEP OUT OF REACH OF CHILDREN

1. Keep out of reach of babies and children

INDICATIONS & USAGE

Indications & Usage: Open the container cap and press the spray button(1~2 times)

DOSAGE & ADMINISTRATION

Dosage & Administration: Do not use more than 5㎖ per day (50 times)